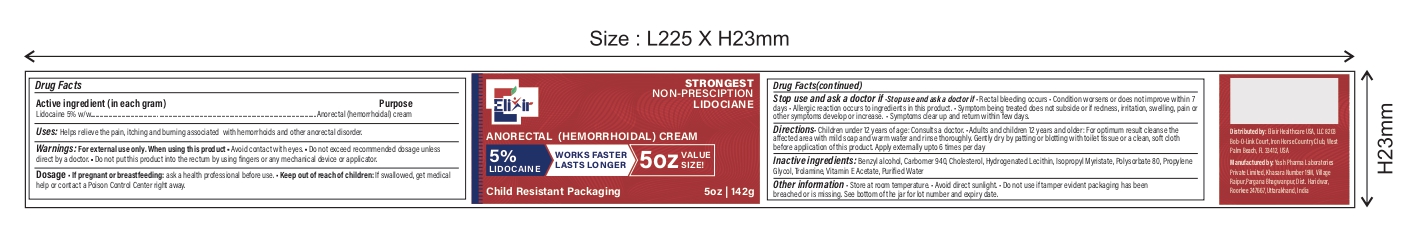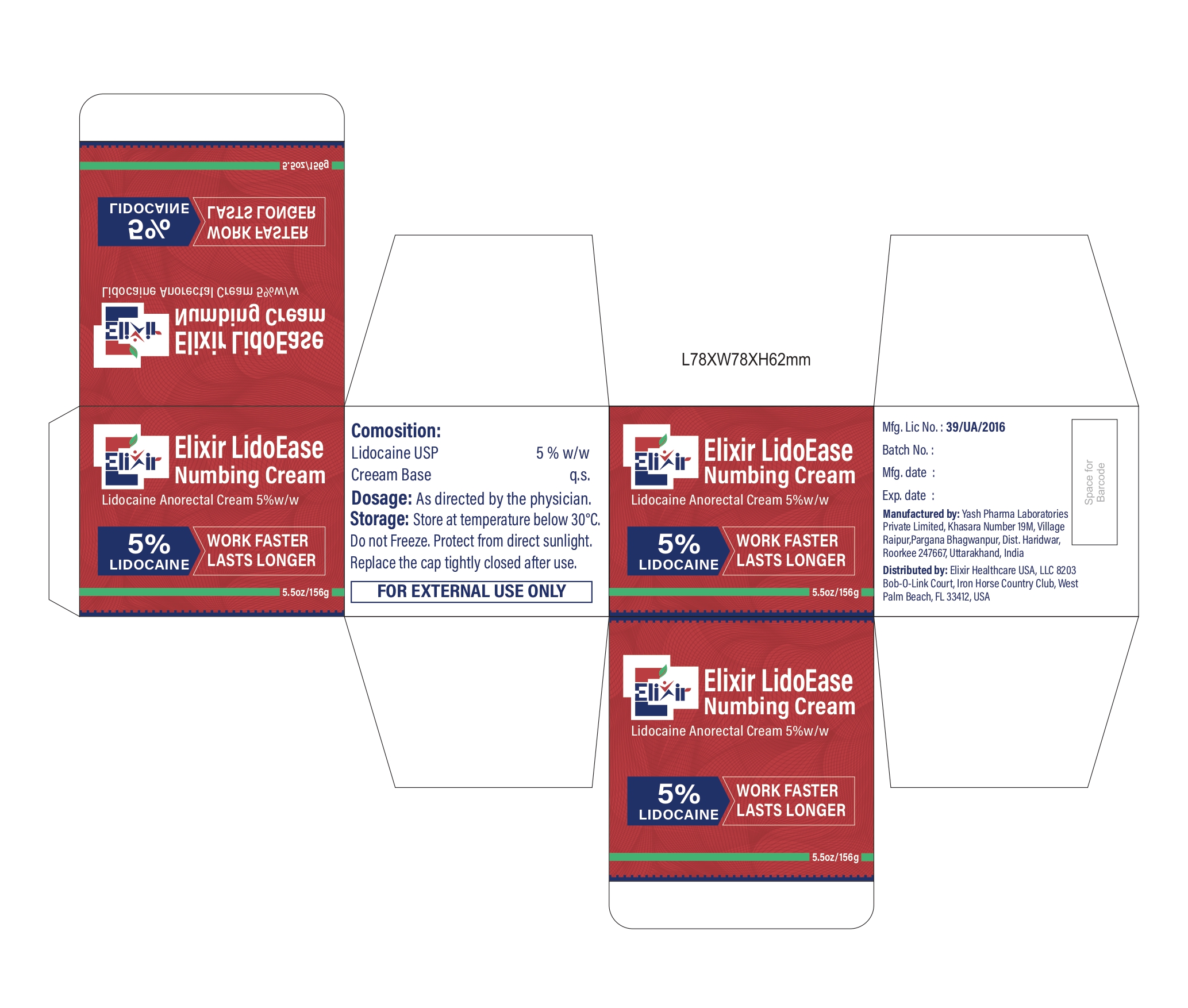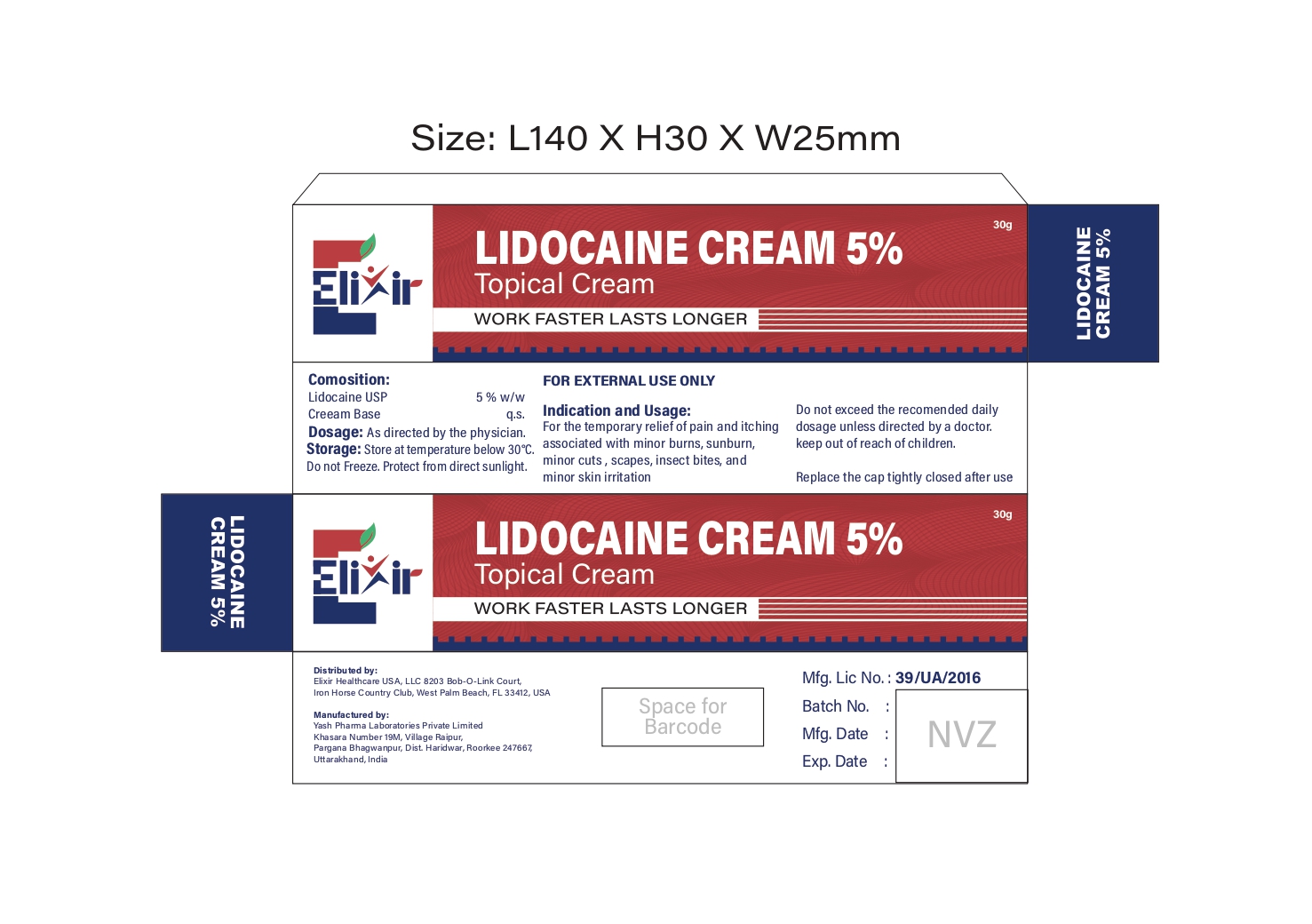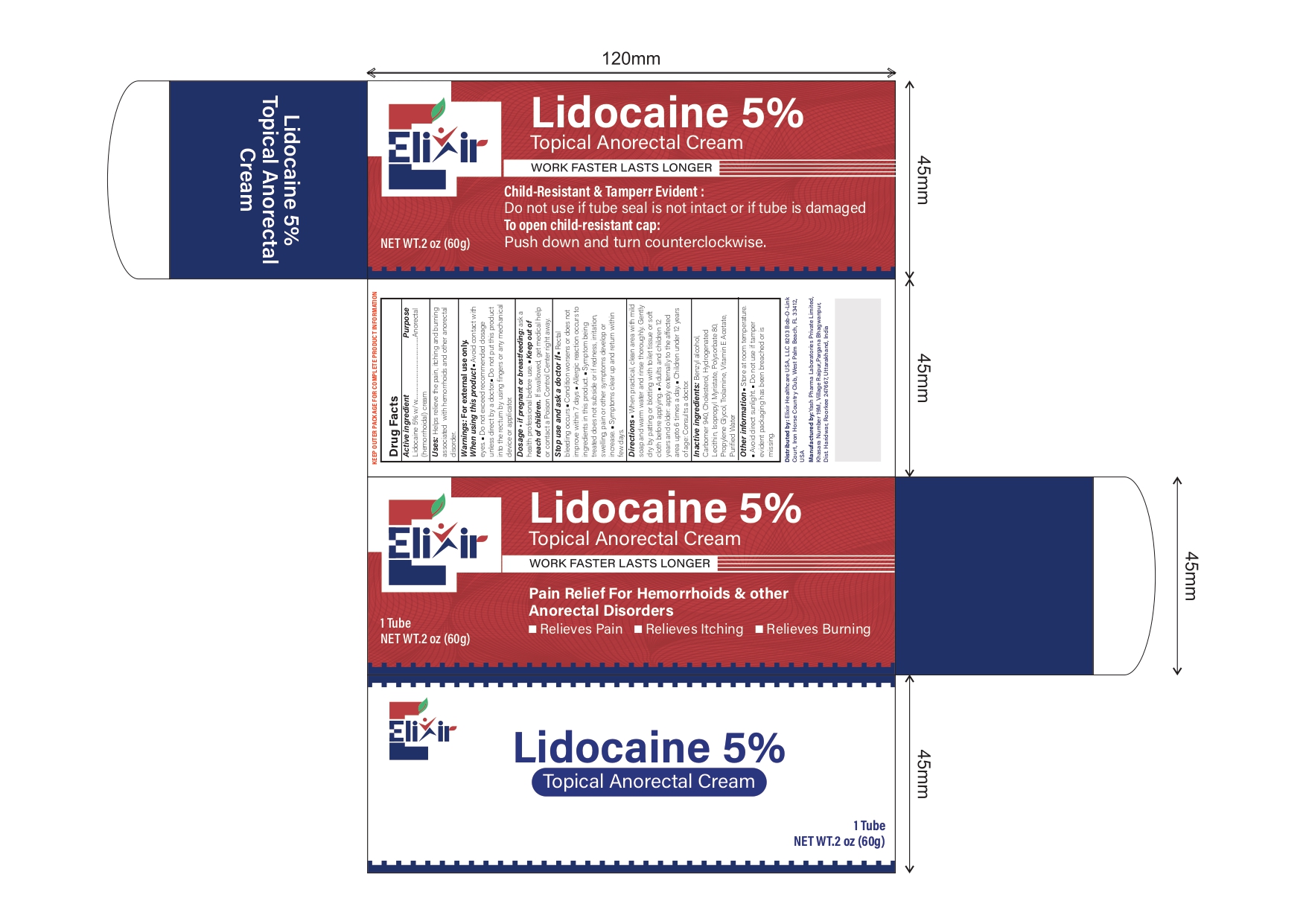 DRUG LABEL: ElixirLidoFast
NDC: 84546-0010 | Form: CREAM
Manufacturer: ELIXIR HEALTHCARE USA, LLC.
Category: otc | Type: HUMAN OTC DRUG LABEL
Date: 20251213

ACTIVE INGREDIENTS: LIDOCAINE 0.05 g/1 g
INACTIVE INGREDIENTS: BENZYL ALCOHOL; CARBOMER 940; CHOLESTEROL; LECITHIN, SOYBEAN; ISOPROPYL MYRISTATE; POLYSORBATE 80; PROPYLENE GLYCOL; TROLAMINE; .ALPHA.-TOCOPHEROL ACETATE

ElixirLidoFast Lidocaine 5% Cream

Active Ingredient (in each gram)

Lidocaine 5% w/w

Purpose

Anorectal (hemorrhoidal) cream

Uses

Helps relieve the pain, itching and burning associated with hemorrhoids and other anorectal disorder.

Warnings:

• For external use only

When using this product,

• Avoid contact with eyes.
• Do not exceed recommended dosage unless direct by a doctor.
• Do not put this product into the rectum by using fingers or any mechanical device or applicator.

Dosage

• If pregnant or breastfeeding: ask a health professional before use.

Stop use and ask a doctor if

• rectal bleeding occurs
• Condition worsens or does not improve within 7 days
• Allergic reaction occurs to ingredients in this product.
• Symptom being treated does not subside or if redness, irritation, swelling, pain or other symptoms develop or increase.
• Symptoms clear up and return within few days.

Keep out of reach of children.

If swallowed, get medical help or contact a Poison Control Center right away.

Directions

apply liberally as often as necessary
For diaper rash:
• change wet or soiled diapers promptly
• cleanse the diaper area and allow to dry
• apply ointment liberally, as often as necessary, with each diaper change and especially at bedtime or anytime when exposure to wet diapers may be prolonged

Inactive ingredients

Benzyl alcohol, Carbomer 940, Cholesterol, Hydrogenated Lecithin, Isopropyl Myristate, Polysorbate 80, Propylene Glycol, Trolamine, Vitamin E Acetate, Purified Water

Other information

• Store at temperature below 30°C.
• Do not freeze. Protect from direct sunlight.

Packaging label for the tube 30g

Elixir

LINDOCAINE CREAM 5%

Topical Cream

WORK FASTER LASTS LONGER

Packaging label for the tube 60g

Elixir

LINDOCAINE CREAM 5%

Topical Anorectal Cream

WORK FASTER LASTS LONGER

Pian Relife For Hemorrhoids & other

Anorectal Disorders

Relieves Pian, Relieves Itching, Relieves Burining

1 Tube Net WT.2 oz (60g)

Packaging label for the Jar 142g

Elixir

STONGEST

NON-PRESCIPTION

LINDOCIANE

ANORECTAL (HEMORRHOIDAL) CREAM

5% LINDOCAINE, WORKS FASTER LASTS LONGER 5oz VALUE SIZE!

Child Resistant Packaging

5oz| 142g

Packaging label for the Jar 156g

Elizir LdioEase Numbing Cream

Lindocaine Anorectal Cream 5% w/w

5% LIDOCAINE

WORK FASTER LASTS LONGER

5.5oz|156g